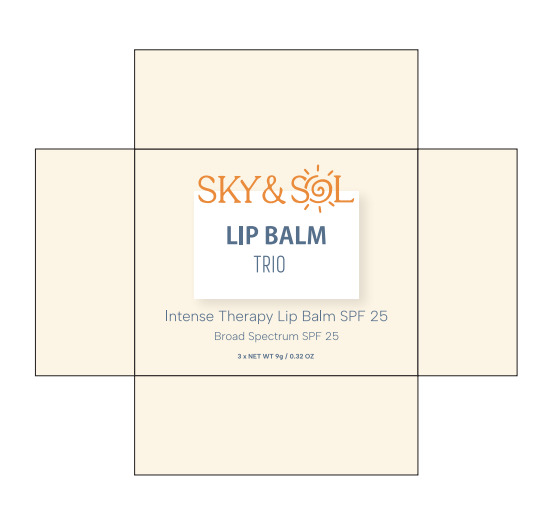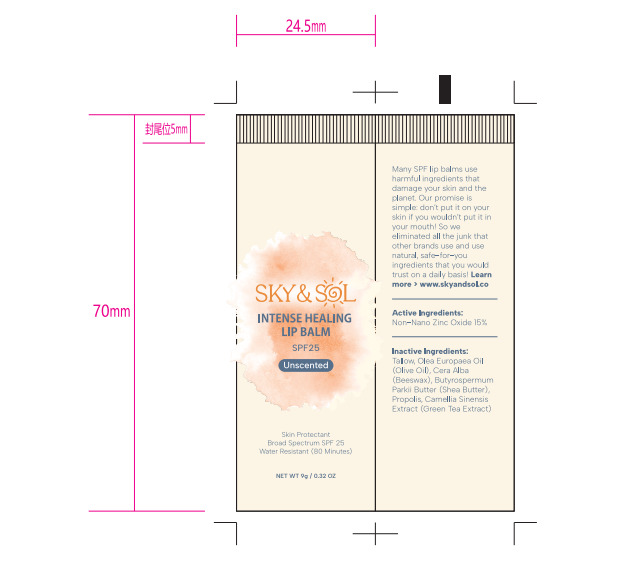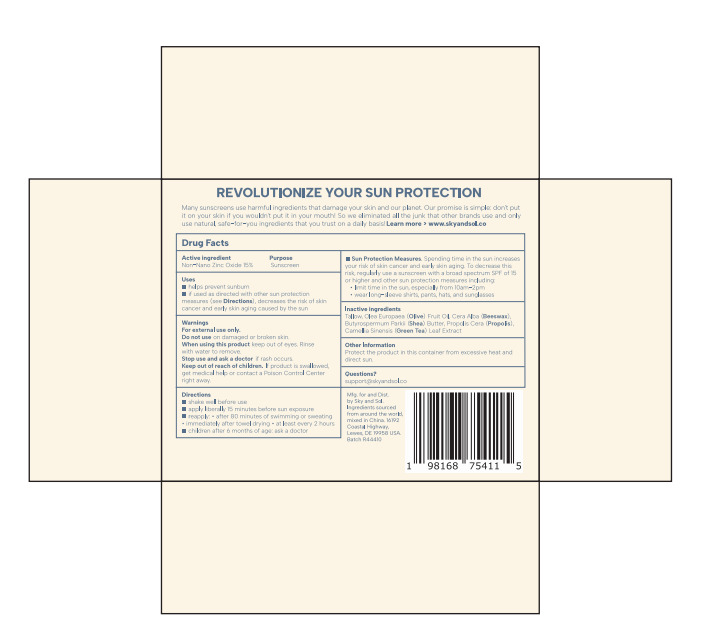 DRUG LABEL: Sky and Sol SPF25 Lip Balm
NDC: 83447-009 | Form: PASTE
Manufacturer: Guangzhou Fantesy Biotechnology Co.,Ltd
Category: otc | Type: HUMAN OTC DRUG LABEL
Date: 20260105

ACTIVE INGREDIENTS: ZINC OXIDE 15 g/100 g
INACTIVE INGREDIENTS: BEEF TALLOW; OLIVE OIL; YELLOW WAX; SHEA BUTTER; PROPOLIS WAX; GREEN TEA LEAF

83447-009

ACTIVE INGREDIENT

Non-Nano Zinc Oxide 15%

PURPOSE

sunscreen

Uses

■helps prevent sunburn
■if used as directed with other sun protection measures (see Directions), decreases the risk of skin cancer and early
skin aging caused by the sun

Warnings

① For external use only.

② When using this product keep out of eyes. Rinse with water to remove.
③ Stop use and ask a doctor if rash occurs.

Do not use on damaged or broken skin.

Keep out of reach of children. If product is swallowed, get medical help or contact a Poison Control Center right away.

Directions

■ shake well before use apply liberally 15 minutes before sun exposure
■ reapply: ●after 80 minutes of swimming or sweating ●immediately after towel drying ●at least every 2 hours
■ children after 6 months of age: ask a doctor

Other information

Protect the product in this container from excessive heat and direct sun.

Inactive Ingredients

Tallow, Olea Europaea (Olive) Fruit Oil, Cera Alba (Beeswax), Butyrospermum Parkii (Shea) Butter, Propolis Cera (Propolis)，
Camellia Sinensis (Green Tea) Leaf Extract